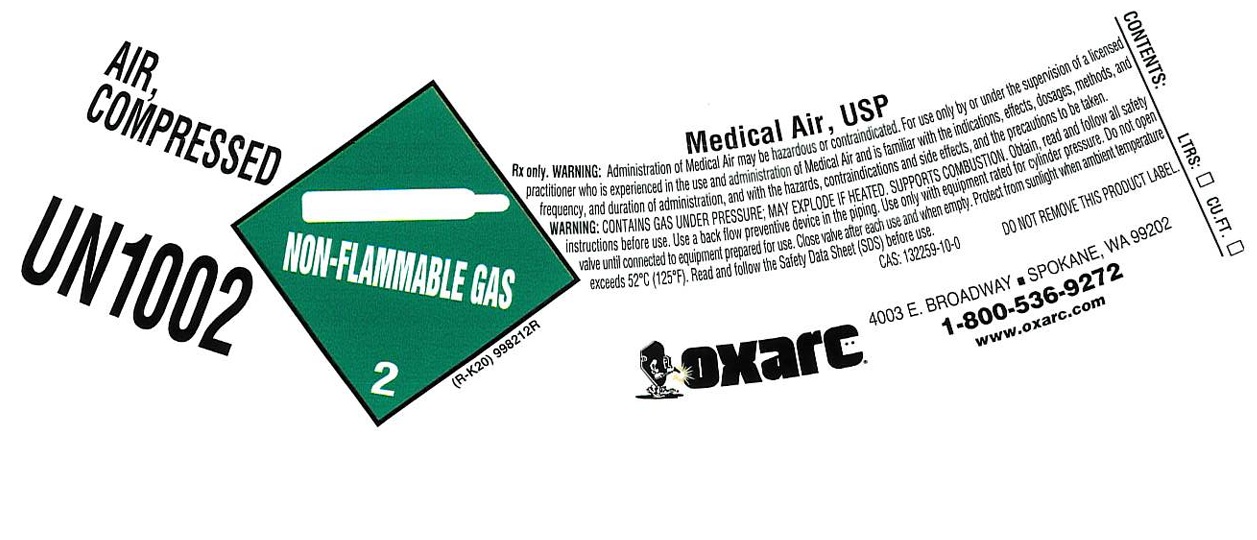 DRUG LABEL: Air
NDC: 34057-016 | Form: GAS
Manufacturer: Oxarc, LLC
Category: animal | Type: PRESCRIPTION ANIMAL DRUG LABEL
Date: 20251125

ACTIVE INGREDIENTS: Air 1000 mL/1 L

air

PACKAGE LABEL

AIR, COMPRESSED
UN1002
Medical Air, USP
Rx only. WARNING: Administration of Medical Air may be hazardous or contraindicated. For use only by or under the supervision of a licensed practitioner who is experienced in the use and administration of Medical Air and is familiar with the indications, effects, dosages, methods, and frequency, and duration of administration, and with the hazards, contraindications and side effects, and the precautions to be taken.
WARNING: CONTAINS GAS UNDER PRESSURE; MAY EXPLODE IF HEATED. SUPPORTS COMBUSTION. Obtain, read and follow all safety instructions before use. Use a back flow preventive device in the piping. Use only with equipment rated for cylinder pressure. Do not open valve until connected to equipment prepared for use. Close valve after each use and when empty. Protect from sunlight when ambient temperature exceeds 52 C (125 F). Read and follow the Safety Data Sheet (SDS) before use.
CAS: 132259-10-0 DO NOT REMOVE THIS PRODUCT LABEL.
OXARC
4003 E. BROADWAY SPOKANE, WA 99202
1-800-536-9272
www.oxarc.com
CONTENTS: LTRS: CU.FT.